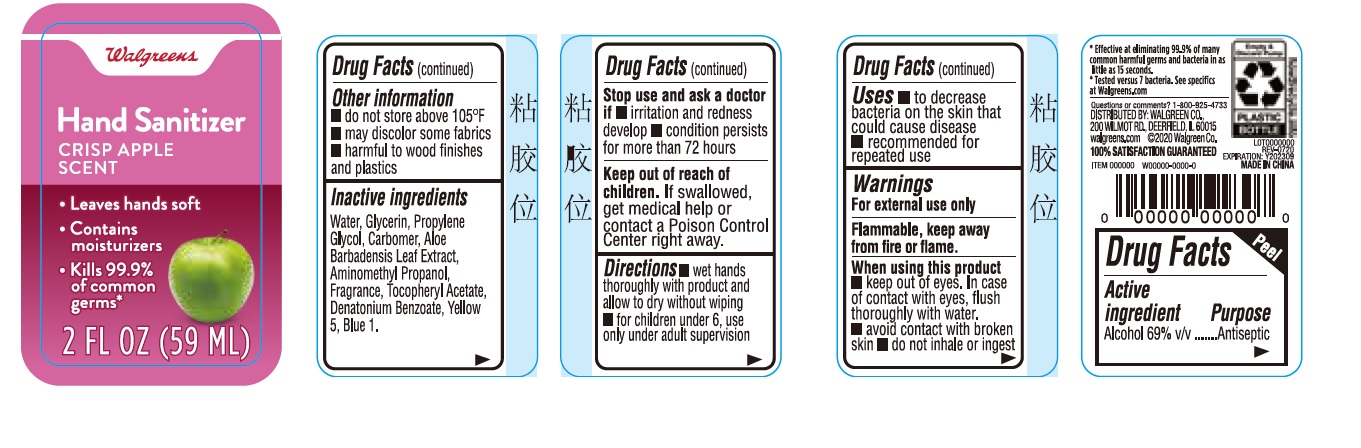 DRUG LABEL: Walgreens Hand Sanitizer Crisp Apple Scent
NDC: 0363-9007 | Form: GEL
Manufacturer: Walgreen Company
Category: otc | Type: HUMAN OTC DRUG LABEL
Date: 20200811

ACTIVE INGREDIENTS: ALCOHOL 69 mL/100 mL
INACTIVE INGREDIENTS: PROPYLENE GLYCOL; DENATONIUM BENZOATE; CARBOMER HOMOPOLYMER, UNSPECIFIED TYPE; ALOE VERA LEAF; AMINOMETHYLPROPANOL; WATER; GLYCERIN; .ALPHA.-TOCOPHEROL ACETATE; FD&C YELLOW NO. 5; FD&C BLUE NO. 1

Walgreens Hand Sanitizer Crisp Apple Scent

Active ingredient

Alcohol 69% v/v

Purpose

Antiseptic

Uses

- to decrease bacteria on the skin that could cause disease
- recommended for repeated use

Warnings

For external use only

Flammable, keep away from fire or flame.

When using this product

- keep out of eyes. In case of contact with eyes, flush thoroughly with water.
- avoid contact with broken skin
- do not inhale or ingest

Stop use and ask a doctor if

- irritation and redness develop
- condition persists for more than 72 hours

Keep out of reach of children.

If swallowed, get medical help or contact a Poison Control Center right away.

Directions

- wet hands thoroughly with product and allow to dry without wiping
- for children under 6, use only under adult supervision

Other information

- do not store above 105F
- may discolor some fabrics
- harmful to wood finishes and plastics

Inactive ingredients

Water, Glycerin, Propylene Glycol, Carbomer, Aloe Barbadensis Leaf Extract, Aminomethyl Propanol, Fragrance, Tocopheryl Acetate, Denatonium Benzoate, Yellow 5, Blue 1.

Company Information

DISTRIBUTED BY: WALGREEN CO.,

200 WILMOT RD., DEERFIELD, IL 60015

Product Packaging

Walgreens

Hand Sanitizer

CRISP APPLE

SCENT

- Leaves hands soft
- Contains moisturizers
- Kills 99.9% of common germs

2 FL OZ (59 ML)